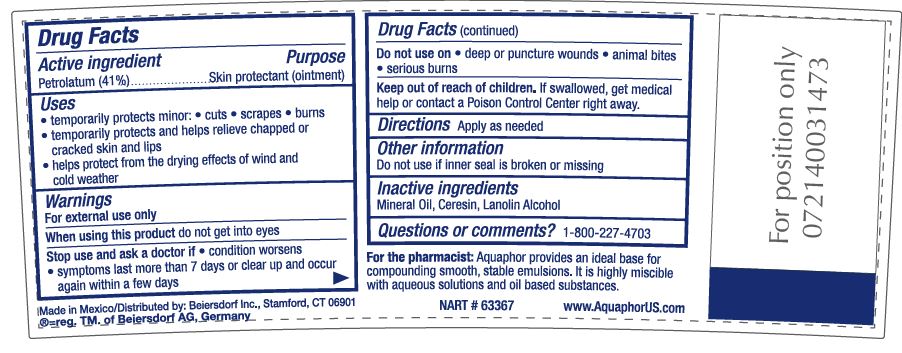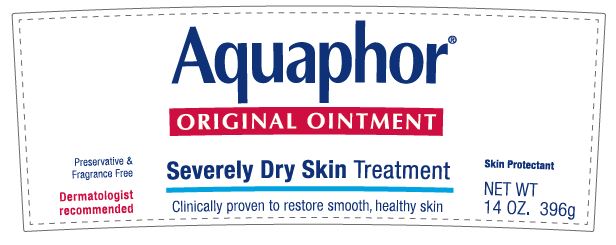 DRUG LABEL: Aquaphor Original
NDC: 10356-100 | Form: OINTMENT
Manufacturer: Beiersdorf Inc
Category: otc | Type: HUMAN OTC DRUG LABEL
Date: 20251215

ACTIVE INGREDIENTS: PETROLATUM 41 g/100 g
INACTIVE INGREDIENTS: MINERAL OIL; CERESIN; LANOLIN ALCOHOLS

Aquaphor Original Ointment

ACTIVE INGREDIENT

Petrolatum 41%

Purpose

Skin Protectant Ointment

Uses

• temporarily protects minor: • cuts • scrapes • burns
• temporarily protects and helps relieve chapped or cracked skin and lips
• helps protect from the drying effects of wind and cold weather

Warnings

For external use only

When using this product • do not get into eyes

Do not use on

• deep or puncture wounds • animal bites
• serious burns

Stop use and ask a doctor if • condition worsens
• symptoms last more than 7 days or clear up and occur
again within a few days

Keep out of reach of children. If swallowed, get medical help
or contact a Poison Control Center right away.

INACTIVE INGREDIENT

Mineral Oil, Ceresin, Lanolin Alcohol

Questions or comments?
1-800-227-4703

Directions

Apply as needed

PACKAGE LABEL

Aquaphor Original Ointment

Severly Dry Skin Treatment

Clinically proven to restore smooth, healthy skin

Preservative and Fragrance Free

Skin Protectant

Dermatologist recommended

For the pharmacist: Aquaphor provides an ideal base for compounding smooth, stable emulsions.

It is highly miscible with aqueous solutions as well as oil-based substances.